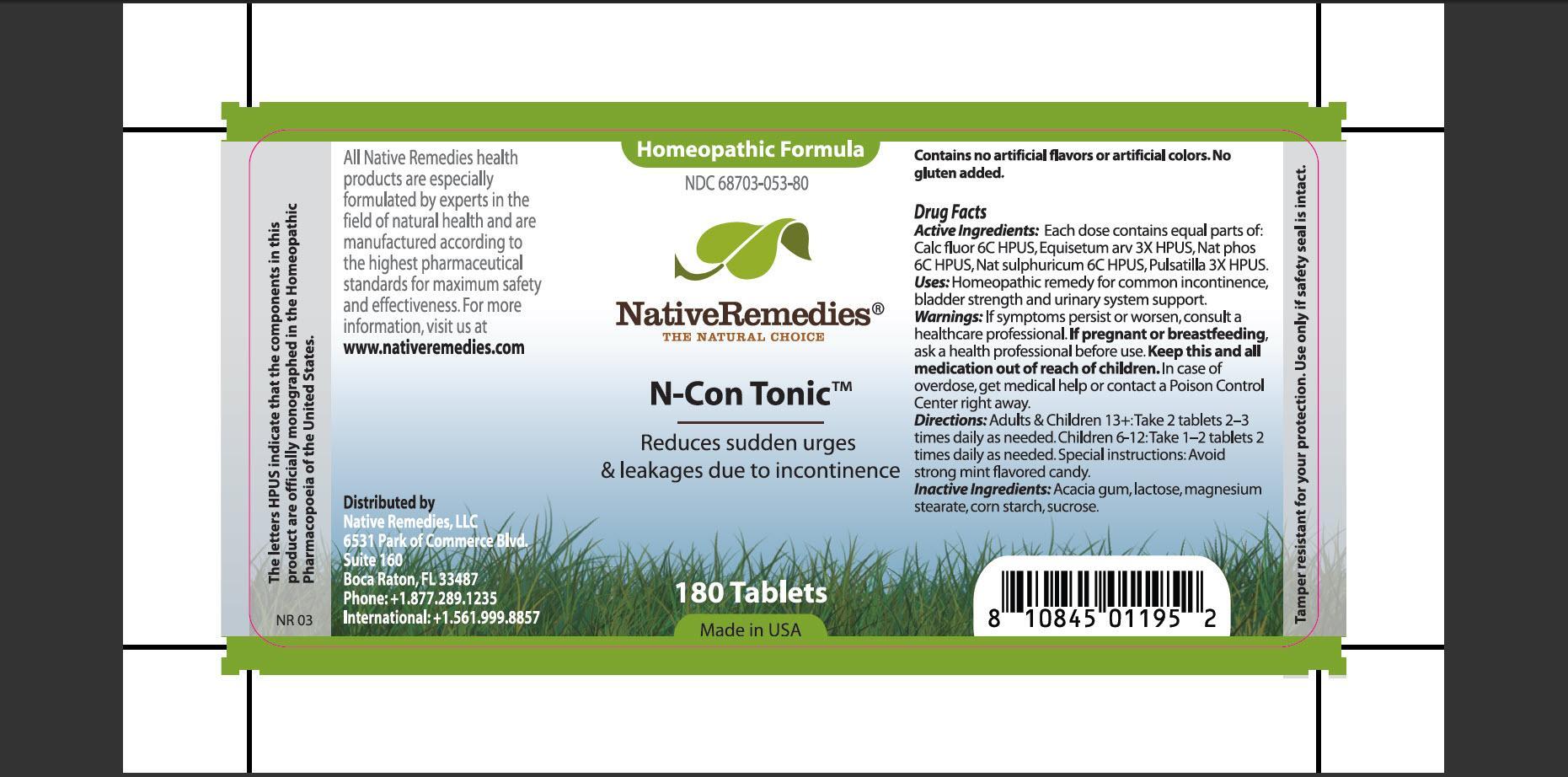 DRUG LABEL: N-Con Tonic
NDC: 68703-053 | Form: TABLET
Manufacturer: Native Remedies, LLC
Category: homeopathic | Type: HUMAN OTC DRUG LABEL
Date: 20130116

ACTIVE INGREDIENTS: CALCIUM FLUORIDE 6 [hp_C]/1 1; EQUISETUM ARVENSE TOP     3 [hp_X]/1 1; SODIUM PHOSPHATE, DIBASIC, HEPTAHYDRATE 6 [hp_C]/1 1; SODIUM SULFATE 6 [hp_C]/1 1; PULSATILLA VULGARIS 3 [hp_X]/1 1
INACTIVE INGREDIENTS: ACACIA; LACTOSE; MAGNESIUM STEARATE; STARCH, CORN; SUCROSE

N-Con Tonic

PURPOSE

Reduce sudden urges and leakages due to incontinence

ACTIVE INGREDIENT

Active Ingredients: Each dose contains equal parts of: Calc fluor 6C HPUS, Equisetum arv 3X HPUS, Nat phos 6C HPUS, Nat sulphuricum 6C HPUS, Pulsatilla 3X HPUS.

INDICATIONS AND USAGE

Uses: Homeopathic remedy for common incontinence, bladder strength and urinary system support.

WARNINGS

Warning: If symptoms persist or worsen, consult a healthcare professional.

PREGNANCY OR BREAST FEEDING

If pregnant or breastfeeding, ask a health professional before use.

KEEP OUT OF REACH OF CHILDREN

Keep this and all medication out of reach of children.

OVERDOSAGE

In case of overdose, get medical help or contact a Poison Control Center right away.

DOSAGE AND ADMINISTRATION

Directions: Adults and Children 13+:Take 2 tablets 2-3 times daily as needed. Children 6-12:Take 1-2 tablets 2 times daily as needed. Special instructions: Avoid strong mint flavored candy.

INACTIVE INGREDIENT

Inactive Ingredients: Acacia gum, lactose, magnesium stearate, corn starch, sucrose.

PATIENT COUNSELING INFORMATION

The letters HPUS indicate that the components in this product are officially monographed in the Homeopathic Pharmacopoeia of the United States.

All Native Remedies health produces are specially formulated by experts in the field of natural health and are manufactured according to the highest pharmaceutical standards for maximum safety and effectiveness. For more information, visit us at www.nativeremedies.com

Distributed by
Native Remedies, LLC
6531 Park of Commerce Blvd.
Suite 160
Boca Raton, Fl 33487
Phone:+1.877.289.1235
International:+1.561.999.8857

Contains no artificial flavors or artificial colors. No gluten added.

STORAGE AND HANDLING

Tamper resistant for your protection. Use only if safety seal is intact.